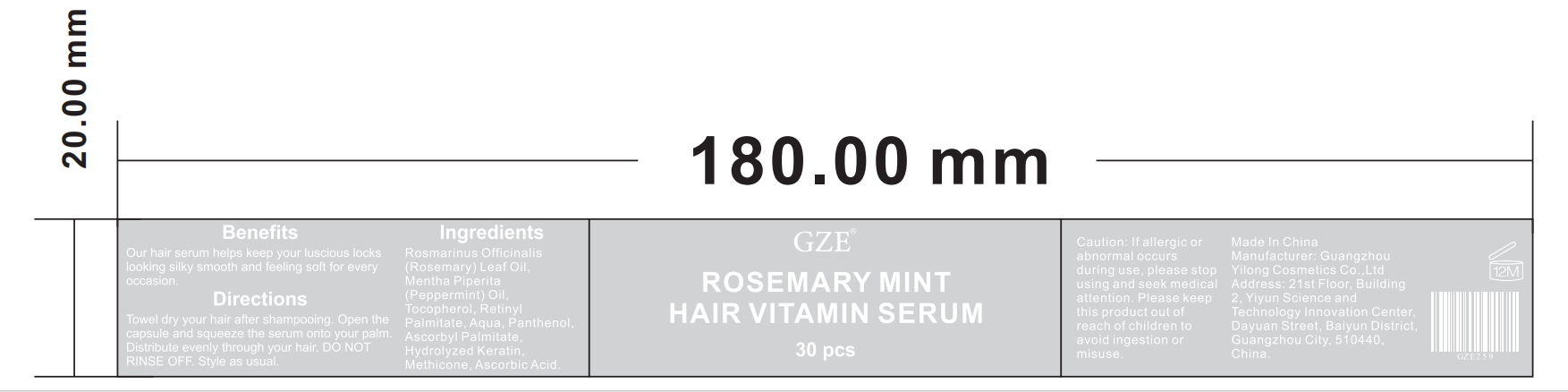 DRUG LABEL: GZE ROSEMARY MINT HAIR VITAMIN SERUM
NDC: 74458-259 | Form: CAPSULE
Manufacturer: Guangzhou Yilong Cosmetics Co., Ltd
Category: otc | Type: HUMAN OTC DRUG LABEL
Date: 20241009

ACTIVE INGREDIENTS: ROSEMARY OIL 40.6 g/100 g
INACTIVE INGREDIENTS: ASCORBIC ACID; WATER; PANTHENOL; ASCORBYL PALMITATE; TOCOPHEROL; PEPPERMINT OIL; METHICONE (20 CST); VITAMIN A PALMITATE; COCODIMONIUM HYDROXYPROPYL HYDROLYZED KERATIN (1000 MW)

GZE ROSEMARY MINT HAIR VITAMIN SERUM

ACTIVE INGREDIENT

Rosemary Oil 46%
Vitamin A Palmitate 0.84%

INACTIVE INGREDIENT

Mentha Piperita(Peppermint) Oil

Tocopherol

Aqua

Panthenol

Ascorbyl Palmitate

Hydrolyzed Keratin

Methicone

Ascorbic Acid

INDICATIONS AND USAGE

Towel dry your hair after shampooing. Open the capsule and squeeze the serum onto your palm. Distribute evenly through your hair. DO NOT RINSE OFF. Style as usual.

PURPOSE

Our hair serum helps keep your luscious locks looking silky smooth and feeling soft for every occasion.

Do not use on damaged or broken skin.

WARNINGS

For external use only.

Stop use and ask a doctor if rash occurs.

When using this product keep out of eyes. Rinse with water to remove.

Keep out of reach of children. If swallowed, get medical help or contact a Poison Control Center right away.

DOSAGE AND ADMINISTRATION

Towel dry your hair after shampooing. Open the capsule and squeeze the serum onto your palm. Distribute evenly through your hair. DO NOT RINSE OFF. Style as usual.